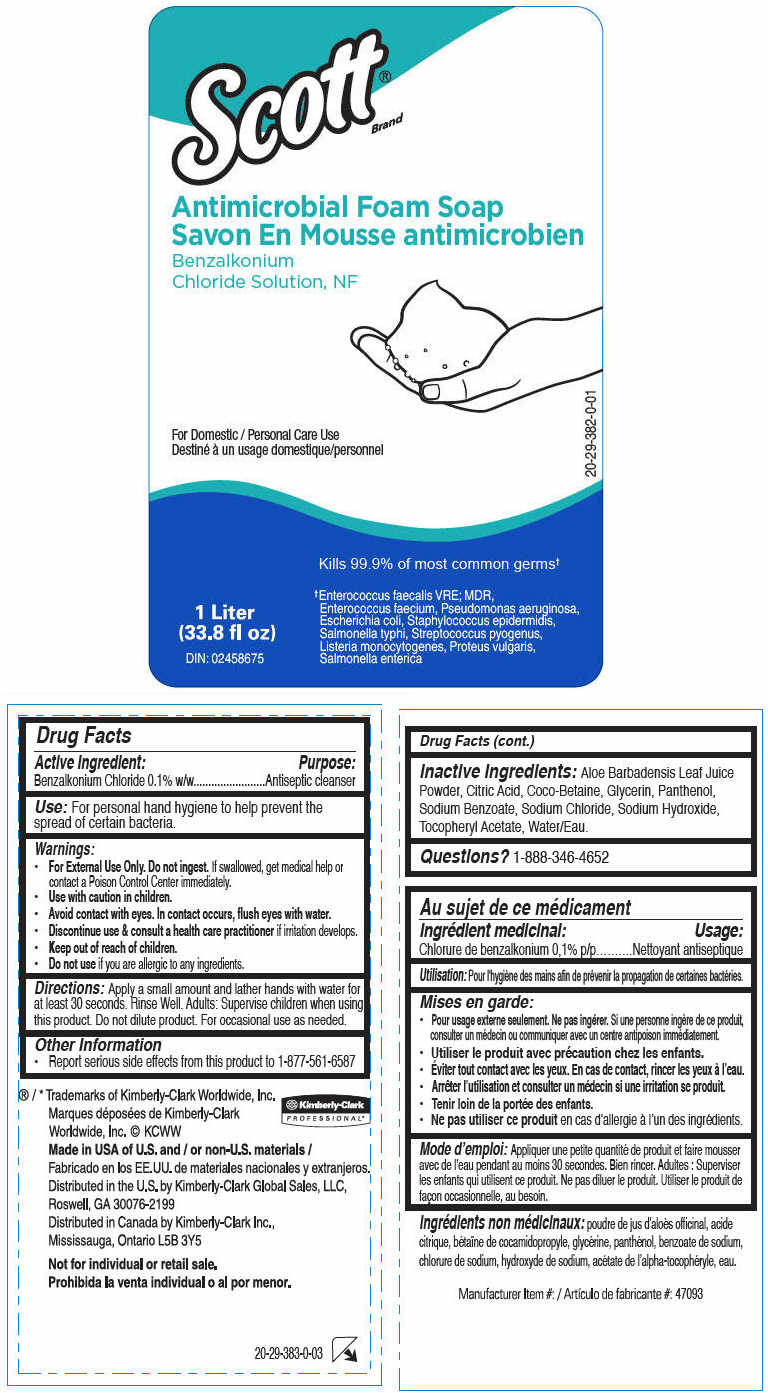 DRUG LABEL: SCOTT Antimicrobial Foam
NDC: 55118-235 | Form: SOLUTION
Manufacturer: Kimberly-Clark
Category: otc | Type: HUMAN OTC DRUG LABEL
Date: 20191016

ACTIVE INGREDIENTS: Benzalkonium Chloride 1 mg/1000 mL
INACTIVE INGREDIENTS: Water; Coco-Betaine; Glycerin; Sodium Chloride; Sodium Benzoate; Citric Acid Monohydrate; Aloe; Panthenol; .Alpha.-Tocopherol Acetate; Sodium Hydroxide

SCOTT® Antimicrobial Foam Soap

Drug Facts

Active Ingredient

Benzalkonium Chloride 0.1% w/w

Purpose

Antiseptic cleanser

Use

For personal hand hygiene to help prevent the spread of certain bacteria.

Warnings

- For External Use Only. Do not ingest. If swallowed, get medical help or contact a Poison Control Center immediately.
- Use with caution in children.
- Avoid contact with eyes. In contact occurs, flush eyes with water.
- Discontinue use & consult a health care practitioner if irritation develops.

- Keep out of reach of children.

- Do not use if you are allergic to any ingredients.

Directions

Apply small amount and lather in hands for at least 30 seconds.

Adults: Supervise children when using this product. Do not dilute product. For occasional use as needed.

Other Information

- Report serious side effects from this product to 1-877-561-6587

Inactive Ingredients

Aloe Barbadensis Leaf Juice Powder, Citric Acid, Coco-Betaine, Glycerin, Panthenol, Sodium Benzoate, Sodium Chloride, Sodium Hydroxide, Tocopheryl Acetate, Water/Eau.

Questions?

1-888-346-4652

Distributed in the U.S. by Kimberly-Clark Global Sales, LLC,
Roswell, GA 30076-2199

PRINCIPAL DISPLAY PANEL - 33.8 fl oz Bottle Label

Scott®
Brand

Antimicrobial Foam Soap

Benzalkonium
Chloride Solution, NF

For Domestic / Personal Care Use

Kills 99.9% of most common germs†

1 Liter
(33.8 fl oz)

DIN: 02458675

†Enterococcus faecalis VRE; MDR,
Enterococcus faecium, Pseudomonas aeruginosa,
Escherichia coli, Staphylococcus epidermidis,
Salmonella typhi, Streptococcus pyogenus,
Listeria monocytogenes, Proteus vulgaris,
Salmonella enterica

20-29-382-0-01